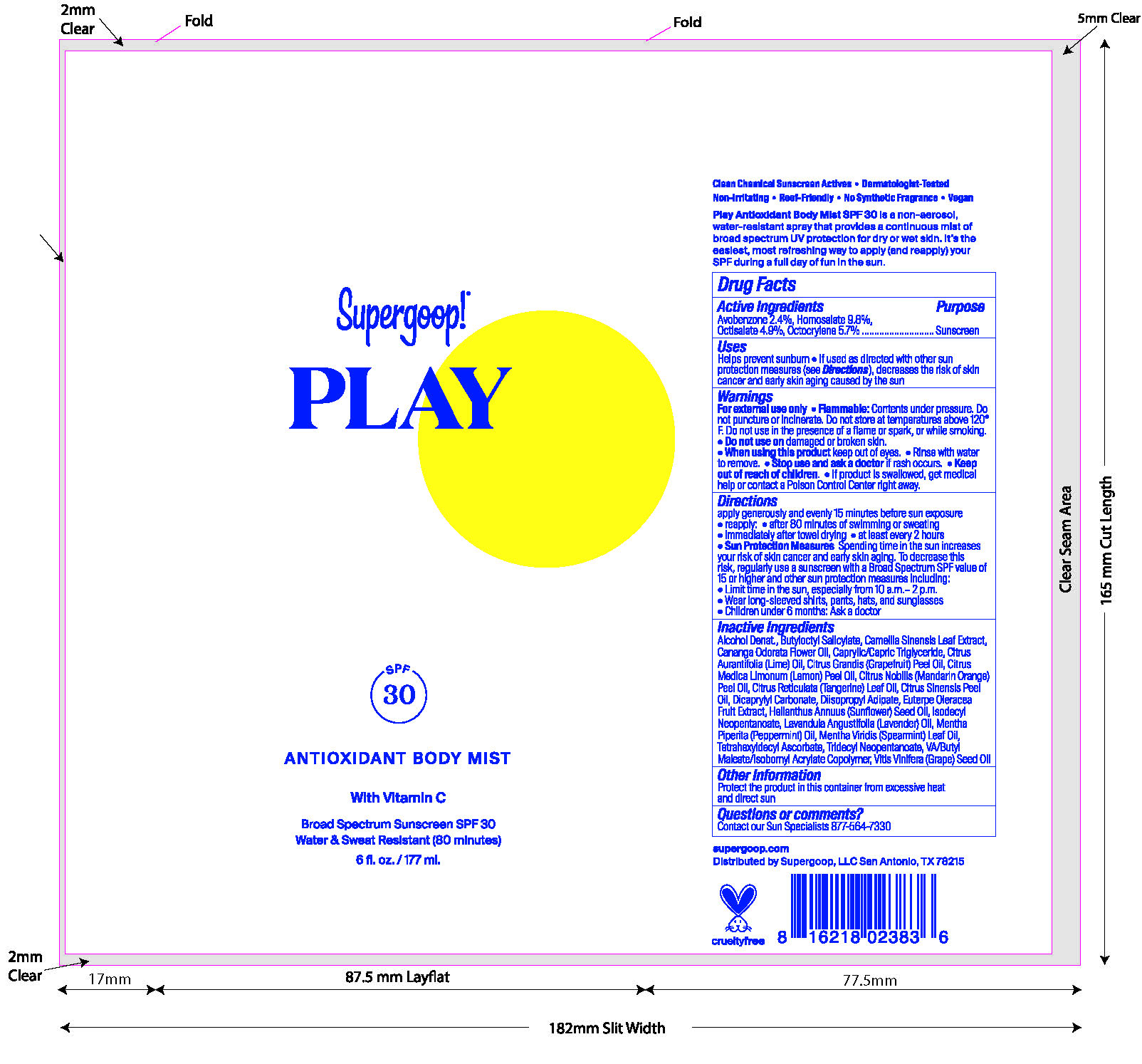 DRUG LABEL: Play Antioxidant Body Mist WIth Vitamin C Broad Spectrum SPF 30
NDC: 75936-668 | Form: SPRAY
Manufacturer: Supergoop, LLC
Category: otc | Type: HUMAN OTC DRUG LABEL
Date: 20251204

ACTIVE INGREDIENTS: HOMOSALATE 9.8 g/100 mL; OCTISALATE 4.9 g/100 mL; OCTOCRYLENE 5.7 g/100 mL; AVOBENZONE 2.4 g/100 mL
INACTIVE INGREDIENTS: MEDIUM-CHAIN TRIGLYCERIDES; LIME OIL; GRAPE SEED OIL; ISODECYL NEOPENTANOATE; CITRUS RETICULATA LEAF OIL; DICAPRYLYL CARBONATE; GREEN TEA LEAF; LEMON OIL; ACAI; SUNFLOWER OIL; BUTYLOCTYL SALICYLATE; PEPPERMINT OIL; TRIDECYL NEOPENTANOATE; CITRUS MAXIMA FRUIT RIND OIL; MANDARIN OIL; ORANGE OIL TERPENELESS; ALCOHOL; CANANGA OIL; TETRAHEXYLDECYL ASCORBATE; DIISOPROPYL ADIPATE; LAVENDER OIL; SPEARMINT OIL; ISOBORNYL ACRYLATE

Play Antioxidant Body Mist WIth Vitamin C Broad Spectrum SPF 30

Active Ingredients Purpose

Avobenzone 2.4% Sunscreen

Homosalate9.8% Sunscreen

Octisalate 4.9% Sunscreen

Octocrylene 5.7% Sunscreen

Uses

Helps prevent sunburn

If used as directed with other sun protection measures (see Directions), decreases the risk of skin cancer and early skin aging caused by the sun.

Keep out of reach of children.

If product is swallowed, get medical help or contact a Poison Control Center right away.

Stop use and ask a doctor is rash occurs.

Warnings

- For external use only
- Flammable: Contents under pressure.Do not puncture or incinerate. Do not store at temperatures above 120 º F. Do not use in the presence of a flame or spark, ow while smoking.
- Do not use on damaged or broken skin
- When using this product keep out of eyes
- Rinse with water to remove

Directions

- apply generously and evenly 15 minutes before sun exposure

reapply

- after 80 minutes of swimming and sweating
- immediately after towel drying
- at least every 2 hours

Sun Protection Measures Spending time in the sun increases your risk of skin cancer and early skin aging. To decrease this risk, regularly use with a Broad Spectrum SPF value of 15 or higher and other sun protection measures

INACTIVE INGREDIENT

Alcohol Denat., Butyloctyl Salicylate, Camellia Sinensis Leaf Extract, Cananga Odorata Flower Oil, Caprylic/Capric Triglyceride, Citrus Aurantifolia (Lime) Oil, Citrus Grandis (Grapefruit) Peel Oil, Citrus Medica Limonum (Lemon) Peel Oil, Citrus Nobilis (Mandarin Orange) Peel Oil, Citrus Reticulata (Tangerine) Leaf Oil, Citrus Sinensis Peel Oil, Dicaprylyl Carbonate, Diisopropyl Adipate, Euterpe Oleracea Fruit Extract, Helianthus Annuus (Sunflower) Seed Oil, Isodecyl Neopentanoate, Lavandula Angustifolia (Lavender) Oil, Mentha Piperita (Peppermint) Oil, Mentha Viridis (Spearmint) Leaf Oil, Tetrahexyldecyl Ascorbate, Tridecyl Neopentanoate, VA/Butyl Maleate/Isobornyl Acrylate Copolymer, Vitis Vinifera (Grape) Seed Oil

PACKAGE LABEL

Supergoop! PLAY

SPF 30

ANTIOXIDANT BODY MIST

with Vitamin C

Broad Spectrum Sunscreen SPF 30

Water & Sweat Resistant (80 minutes)

6fl. oz.